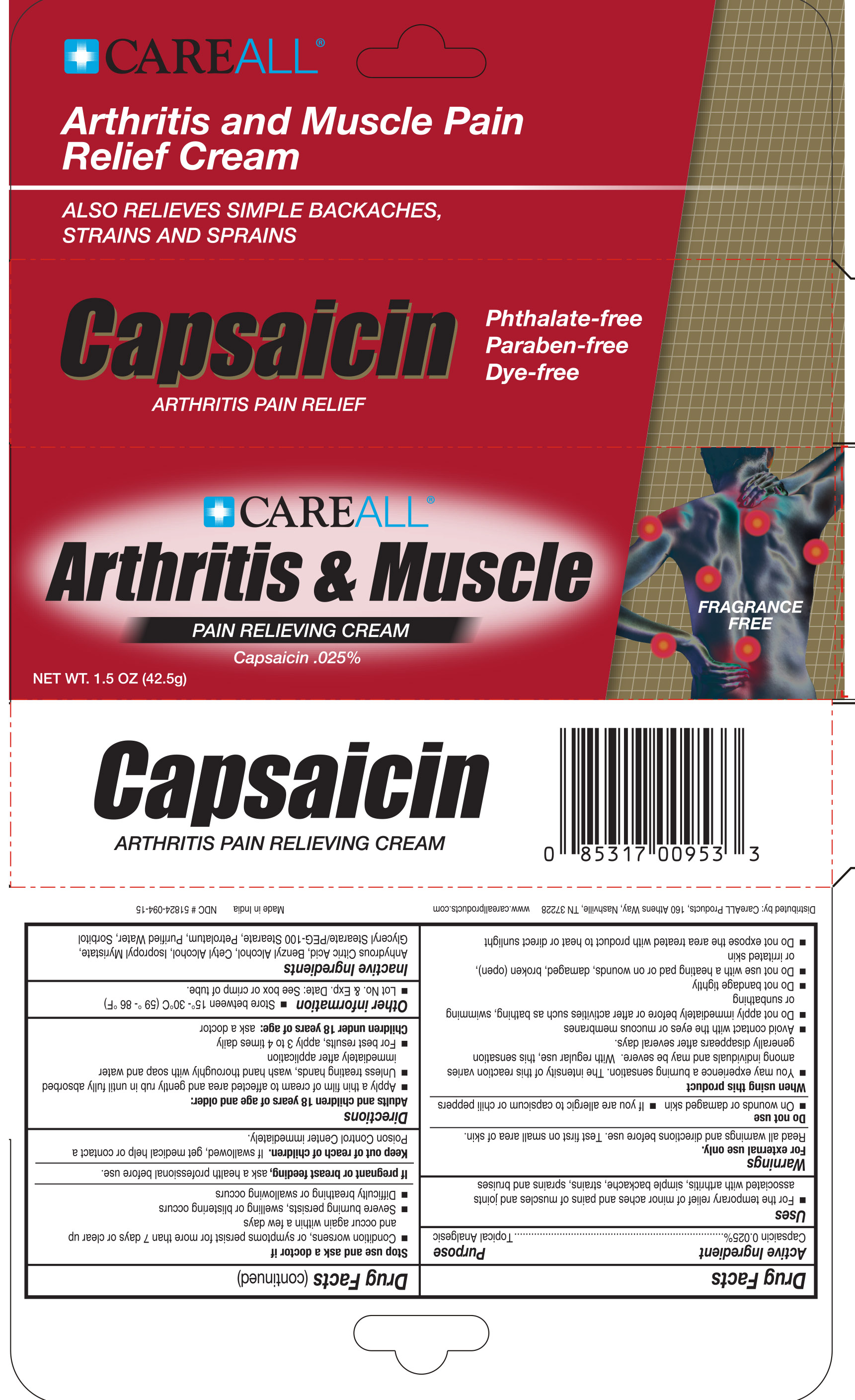 DRUG LABEL: CareALL Arthritis and Muscle
NDC: 51824-094 | Form: CREAM
Manufacturer: New World Imports, Inc
Category: otc | Type: HUMAN OTC DRUG LABEL
Date: 20251201

ACTIVE INGREDIENTS: CAPSAICIN 0.025 g/1 g
INACTIVE INGREDIENTS: BENZYL ALCOHOL; CETYL ALCOHOL; ANHYDROUS CITRIC ACID; GLYCERYL STEARATE/PEG-100 STEARATE; ISOPROPYL MYRISTATE; PETROLATUM; WATER; SORBITOL

Active Ingredient

Capsaicin 0.025%

Purpose

Topical Analgesic

Keep out of Reach of Children. If swallowed, get medical helpor contact a Posion Control Center immediately.

Uses

For the temporary relief of minor aches and pains of muscles and joints associated with arthritis, simple backaches, strains, sprains and bruises

Warnings

For external use only. Read all warnings and directions before use. Test first on small area of skin.

Do not use

- On wounds or damaged skin
- If you are allergic to capsicum or chili peppers

When using this product

- You may experience a burning sensation. The intensity of this reaction varies among individuals and may be severe. With regular use, this sensation generally disappears after several days
- Avoid contact with the eyes or mucous membranes.
- Do no apply immediately before or after activites such as bathing, swimming or sunbathing
- Do not banage tightly
- Do no apply heat to the treated area immediately before or after use
- Do not use with a heating pad or on wounds, damaged, broken (open) or irritated skin
- Do ot expose the area treated with product to heat or direct sunlight

Stop use and ask a doctor if:

- Condition worsens or symptoms persist for more than 7 days or clear up and occur again within a few days
- Severe burning persists, swelling or blistering occurs
- Difficulty breathing or swallowing occurs

If pregnant or breast feeding,ask a health professional before use.

Directions

Adults and children 18 years of age and older:

- Apply a thin film of cream to affected area and gently rub in until fully absorbed
- Unless treating hands, wash hand thoroughly with soap and water immediately after application
- For best results, apply 3 to 4 times daily

Children under 18 years of age:ask a doctor

Inactive Ingredients

Anhydrous Citric Acid, Benzyl Alcohol, Cetyl Alcohol, Glyceryl Stearate/PEG-100 Stearate, Isopropyl Myristate, Petrolatum, Purified Water, Sorbitol